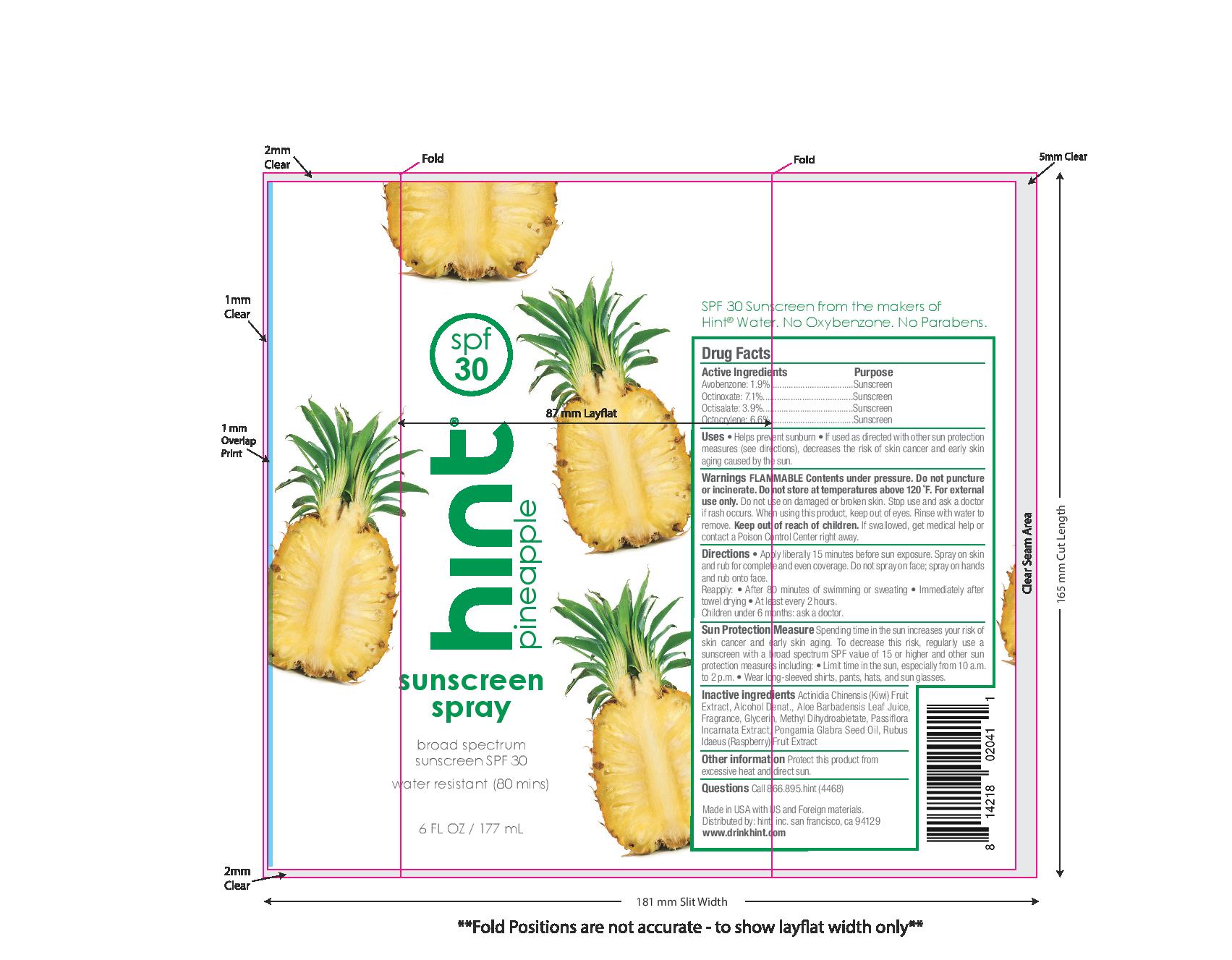 DRUG LABEL: Pineapple
NDC: 76150-206 | Form: AEROSOL
Manufacturer: Bell International Laboratories, Inc.
Category: otc | Type: HUMAN OTC DRUG LABEL
Date: 20210114

ACTIVE INGREDIENTS: OCTISALATE 3.9 g/100 mL; OCTOCRYLENE 6.6 g/100 mL; OCTINOXATE 7.1 g/100 mL; AVOBENZONE 1.9 g/100 mL
INACTIVE INGREDIENTS: GLYCERIN; PASSIFLORA INCARNATA FLOWER; KARUM SEED OIL; METHYL DIHYDROABIETATE; ALCOHOL; RASPBERRY; KIWI FRUIT; ALOE VERA LEAF

Hint SPF 30 Sunscreen Spray Pineapple

Acitve Ingredients

Avobenzone 1.9%, Octinoxate 7.1%, Octisalate 3.9%, Octocrylene 6.6%

Purpose

Sunscreen

Uses

helps prevent sunburn

if used as directed with other sun protection measures (see Directions), decreases the risk of skin cancer and early skin aging caused by the sun

Warnings

Flammable Contents under pressure. Do not puncture or incinerate. Do not store at temperatures above 120 oF.

For external useonly

Do not use on damaged or broken skin.

Stop use and ask a doctor if rash occurs.

When using this product, keep out of eyes. Rinse with water to remove.

Keep out of reach of children. If swallowed, get medical help or contact a Poison Control Center right away.

Directions

Apply liberally 15 minutes before sun exposure. Spray on skin and rub for complete and even coverage. Do not spray on face; spray on hands and rub onto face.

Reapply

- after 80 minutes of swimming or sweating
- immediately after towel drying
- at least every 2 hours

Children under 6 months: Ask a doctor

Sun Protection Measure. Spending time in the sun increases your risk of skin cancer and early skin aging. To decrease this risk, regularly use a sunscreen wtih a broad spectrum SPF value of 15 or higher and other sun protection measures including:

- limit time in the sun, especially from 10am-2pm
- Wear long-sleeved shirts, pants, hats and sun glasses

Inactive ingredients

Actinidia Chinensis (Kiwi) Fruit Extract, Alcohol Denat., Aloe Barbadensis Leaf Juice, Fragrance, Glycerin, Methyl Dihydroabietate, passiflora Incarnata Extract, Pongamia Glabra Seed Oil, Rubus Idaeus (Raspberry) Fruit Extract

Other information

protect this product from excessive heat and direct sun.